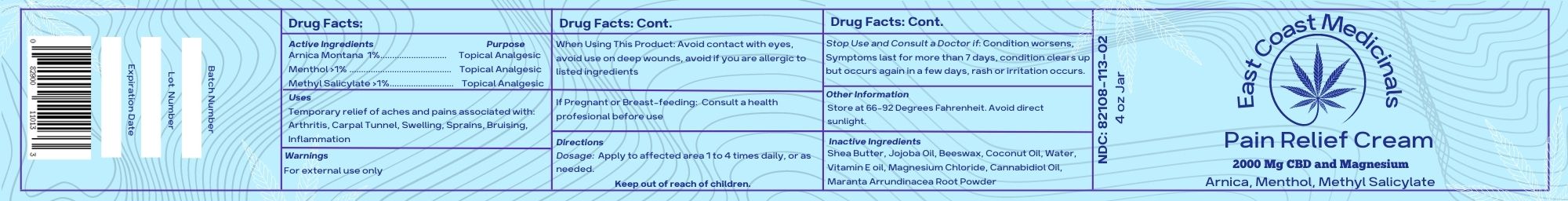 DRUG LABEL: ECM Pain Relief
NDC: 82108-113 | Form: CREAM
Manufacturer: East Coast Medicinals
Category: homeopathic | Type: HUMAN OTC DRUG LABEL
Date: 20221208

ACTIVE INGREDIENTS: ARNICA MONTANA 2.7 g/170.96 g; METHYL SALICYLATE 0.57 g/170.96 g; MENTHOL 0.28 g/170.96 g
INACTIVE INGREDIENTS: WATER 8.79 g/170.96 g; COCONUT OIL 18.43 g/170.96 g; PEG-8 BEESWAX 18.43 g/170.96 g; MAGNESIUM CHLORIDE 4.25 g/170.96 g; ALPHA-TOCOPHEROL 6.52 g/170.96 g; SHEA BUTTER 54 g/170.96 g; CANNABIDIOL 1.42 g/170.96 g; JOJOBA OIL 55 g/170.96 g; MARANTA ARUNDINACEA ROOT 0.57 g/170.96 g

East Coast Pain Releif

Active Ingredients

Arnica Montana (1%)................................ Topical Analgesic

Menthol (>1%).................................................. Topical Analgesic

Methyl Salicylate (>1%) ................................ Topical Analgesic

Uses

Temporary relief of aches and pains associated with: Arthritis, Carpal Tunnel, Swelling, Sprains, Bruising, Inflammation

DOSAGE AND ADMINISTRATION

Dosage: Apply to affected area 1 to 4 times daily, or as needed.

Keep out of reach of children.

WARNINGS

Stop Use and Consult a Doctor if: Condition worsens, Symptoms last for more than 7 days, condition clears up but occurs again in a few days, rash or irritation occurs.

WHEN USING

For external use only

keep pout of reach of children

PREGNANCY

If Pregnant or Breast-feeding: Consult a health profesional before use

INDICATIONS AND USAGE

Dosage: Apply to affected area 1 to 4 times daily, or as needed.

OTHER SAFETY INFORMATION

Store at 66-92 Degrees Fahrenheit. Avoid direct sunlight.

INACTIVE INGREDIENT

Shea Butter, Jojoba Oil, Beeswax, Coconut Oil, Water, Alpha Tocopherol, Magnesium Chloride, Cannabidiol Oil, Maranta Arrundinacea Root Powder